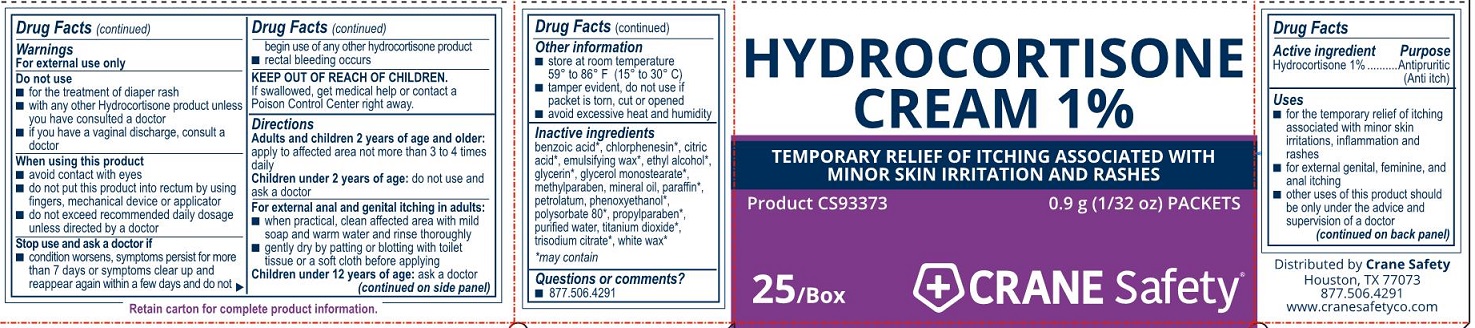 DRUG LABEL: Crane Safety Hydrocortisone
NDC: 73408-933 | Form: CREAM
Manufacturer: Crane Safety LLC
Category: otc | Type: HUMAN OTC DRUG LABEL
Date: 20241105

ACTIVE INGREDIENTS: HYDROCORTISONE 10 mg/1 g
INACTIVE INGREDIENTS: PROPYLPARABEN; MINERAL OIL; PETROLATUM; WATER; ALCOHOL; METHYLPARABEN; PARAFFIN; WHITE WAX

Crane Safety Hydrocortisone Cream

Active ingredient (in each gram)

Hydrocortisone 1.0%

Purpose

Antipruritic (Anti-itch)

Uses

- for the temporary relief of itching associated with minor skin irritation, inflammation and rashes
- for externalgenital,femine and anal itching
- other uses for this product should be only under the advice and supervision of a doctor

Warnings

For external use only

Do not use

- for the teatment of diaper rash
- with any other hydrocortisone product unless you have consulted a doctor
- if you have vaginal discharge, consult a doctor

Stop use and ask a doctor if

- condition worsens, symptoms persist for more than 7 days or symptoms clear up and reappear again within a few days and do not begin use of any other hydrocortisone product
- rectal bleeding occurs

Keep out of reach of children.

If swallowed, get medical help or contact a Poison Control Center right away.

Directions

Adults and children 2 years of age and over:

apply to affected area not more than 3 to 4 times daily

Children under 2 years:

do not use and ask a doctor

For external genital itching in adults:

- when practical, clean affected area with mild soap and warm water and rinse thoroughly
- gently dry by patting or blotting with toilet tissue or a soft cloth before applying

Children under 12 years of age:

ask a doctor

Other information

- store at room temperature 59º to 86ºF (15º to 30ºC)
- tamper evident, do not use if packet is toen, cut or opened
- avoid excessive heat and humidity

Inactive ingredients

benzoic acid*, chlorphenesin*, citric acid*, emulsifying wax*, ethyl alcohol*, glycerin*, glycerol monostearate*, methylparaben, mineral oil, paraffin*, petrolatum, phenoxyethanol*, polysorbate 80*, propylparaben*, purified water, titanium dioxide*, trisodium citrate*, white wax*

May contain*

Questions or comments?

877.506.4291

Crane Safety Hydrocortisone 1% Cream Label

Hydrocortisone Cream 1%

Temporary Relief of Itching Associated With Minor Skin Irritation and Rashes

Product CS93373

0.9 g (1/32 oz) Packets

25/Box

CRANE Safety®

Crane Safety Hydrocortisone Label

Hydrocortisone Cream 1%

Temporary Relief of Itching Associated With Minor Skin Irritation and Rashes

Product CS93373

0.9 g (1/32 oz) Packets

25/Box

CRANE Safety®